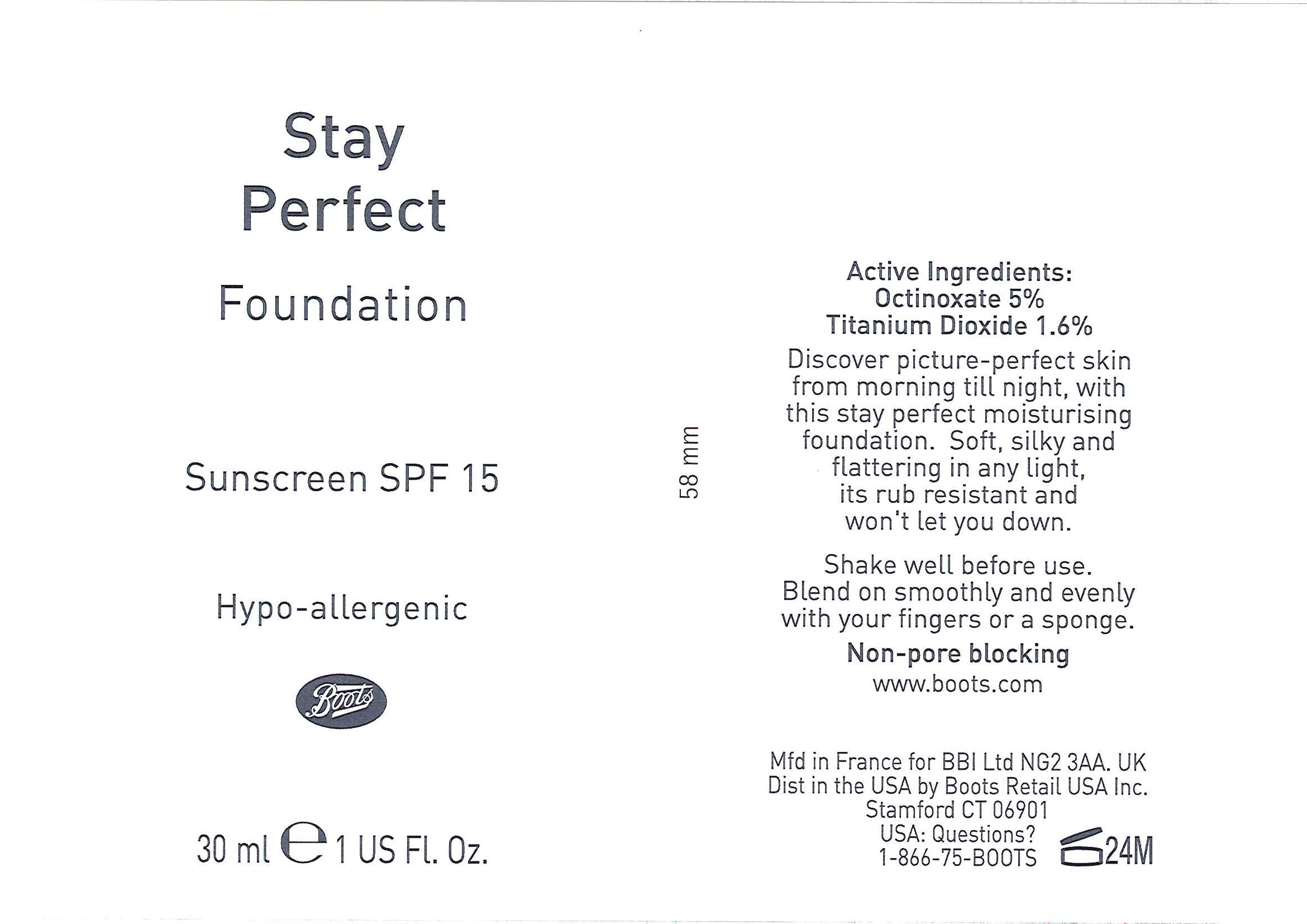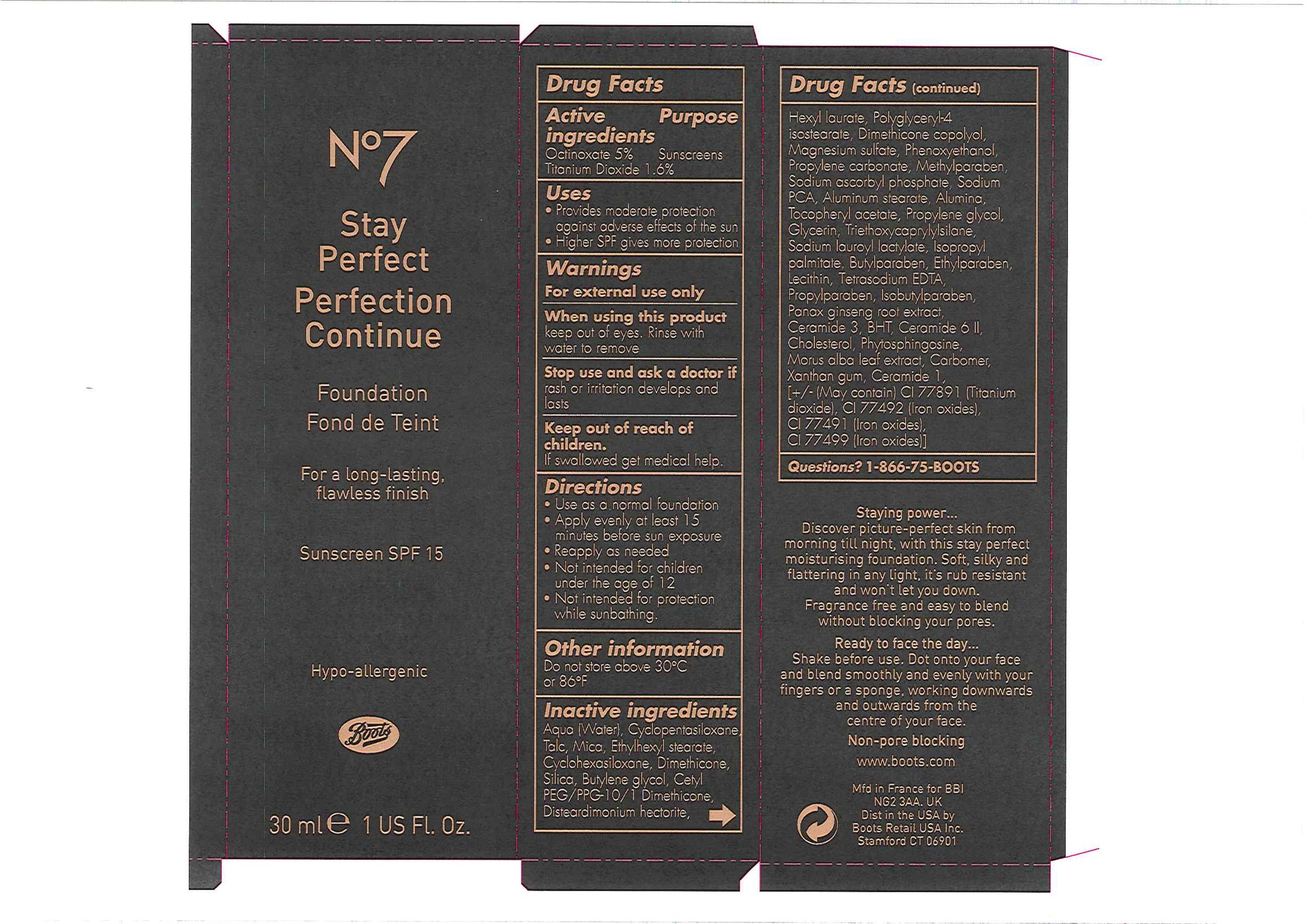 DRUG LABEL: No7 Stay Perfect Foundation Sunscreen SPF 15 Espresso
NDC: 61589-1824 | Form: EMULSION
Manufacturer: BCM Cosmetique SAS
Category: otc | Type: HUMAN OTC DRUG LABEL
Date: 20110110

ACTIVE INGREDIENTS: OCTINOXATE 1.5 mL/30 mL; TITANIUM DIOXIDE 0.48 mL/30 mL
INACTIVE INGREDIENTS: WATER; CYCLOMETHICONE 5; TALC; CYCLOMETHICONE 6; DIMETHICONE; SILICON DIOXIDE; BUTYLENE GLYCOL; HEXYL LAURATE; POLYGLYCERYL-4 ISOSTEARATE; MAGNESIUM SULFATE, UNSPECIFIED; PHENOXYETHANOL; PROPYLENE CARBONATE; METHYLPARABEN; SODIUM ASCORBYL PHOSPHATE; SODIUM PYRROLIDONE CARBOXYLATE; ALUMINUM STEARATE; ALUMINUM OXIDE; .ALPHA.-TOCOPHEROL ACETATE, DL-; PROPYLENE GLYCOL; GLYCERIN; OCTYLTRIETHOXYSILANE; ISOPROPYL PALMITATE; BUTYLPARABEN; ETHYLPARABEN; LECITHIN, SOYBEAN; EDETATE SODIUM; PROPYLPARABEN; ISOBUTYLPARABEN; ASIAN GINSENG; BUTYLATED HYDROXYTOLUENE; CHOLESTEROL; WHITE MULBERRY; CARBOMER HOMOPOLYMER TYPE C; XANTHAN GUM; FERRIC OXIDE YELLOW; FERRIC OXIDE RED; FERROSOFERRIC OXIDE

Carton and bottle labelling

Active Ingredients Purpose

Octinoxate 5% Sunscreens

Titanium Dioxide 1.6%

Uses

- Provides moderate protection against adverse effects of the sun
- Higher SPF gives more protection

Warnings

For external use only

When using this product

Keep out of eyes. Rinse with water to remove.

Stop use and ask a doctor if rash or irritation develops and lasts

Keep out of reach of children.

If swallowed get medical help.

Directions

- Use as a normal foundation
- Apply evenly at least 15 minutes before sun exposure
- Reapply as needed
- Not intended for children under the age of 12
- Not intended for protection while sunbathing

Other information

Do not store above 30oC or 86oF

Inactive ingredients

Aqua (Water), Cyclopentasiloxane, Talc, Mica, Ethylhexyl stearate, Cyclohexasiloxane, Dimethicone, Silica, Butylene glycol, Cetyl PEG/PPG-10/1 Dimethicone, Disteardimonium hectorite, Hexyl laurate, Polyglyceryl-4 isostearate, Dimethicone copolyol, Magnesium sulfate, Phenoxyethanol, Propylene carbonate, Methylparaben, Sodium ascorbyl phosphate, Sodium PCA, Aluminum stearate, Alumina, Tocopheryl acetate, Propylene glycol, Glycerin, Triethoxycaprylylsilane, Sodium lauroyl lactylate, Isopropyl palmitate, Butylparaben, Ethylparaben, Lecithin, Tetrasodium EDTA, Propylparaben, Isobutylparaben, Ceramide 3, BHT, Ceramide 6 II, Cholesterol, Phytosphingosine, Morus alba leaf extract, Carbomer, Xanthan gum, Ceramide 1, [+/1 (May contain) CI 77891 (Titanium dioxide), CI 77492 (Iron oxides), CI 77491 (Iron oxides), CI 77499 (Iron oxides).

Questions? 1-866-75-BOOTS

DESCRIPTION

Staying power...
Discover picture-perfect skin from morning till night, with this stay perfect moisturising foundation. Soft, silky and flattering in any light, it's rub resistant and won't let you down. Fragrance free and easy to blend without blocking your pores.
Ready to face the day...
Shake before use. Dot onto your face and blend smoothly and evenly with your fingers or a sponge, working downwards and outwards from the centre of your face.
Non-pore blocking.

PATIENT COUNSELING INFORMATION

www.boots.com

Mfd in France for BBI NG2 3AA. UK

Dist in the USA by Boots Retail USA Inc Stamford CT 06901

ACTIVE INGREDIENT

Bottle label
Active Ingredients:
Octinoxate 5%
Titanium Dioxide 1.6%

DESCRIPTION

Discover picture-perfect skin from morning till night, with this stay perfect moisturising foundation. Soft, silky and flattering in any light, its rub resistant and won't let you down.
Shake well before use. Blend on smoothly and evenly with your fingers or a sponge.

Non-pore blocking.

PATIENT COUNSELING INFORMATION

www.boots.com

Mfd in France for BBI Ltd NG2 3AA. UK

Dist in the USA by Boots Retail USA Inc. Stamford CT 06901

USA: Questions? 1-866-75-BOOTS

Carton label

No7 Stay Perfect

Perfection Continue

Foundation

Fond de Teint

For a long-lasting flawless finish

Sunscreen SPF 15

Hypo-allergenic

Boots

30ml e 1 US Fl. Oz

Stay Perfect Fdn carton.jpg

PACKAGE LABEL

Stay Perfect

Foundation

Sunscreen SPF 15

Hypo-allergenic

Boots

30ml e 1 US Fl. Oz

Stay Perfect Fdn bottle labels.jpg